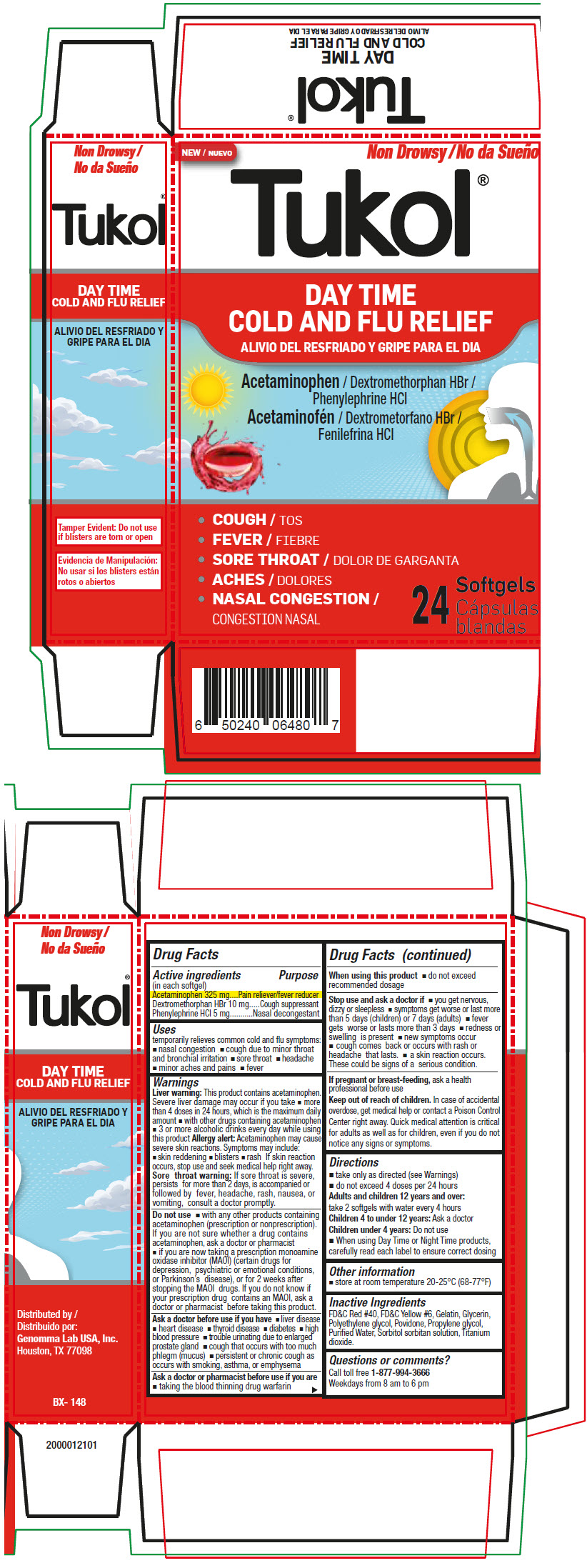 DRUG LABEL: Tukol Day Time Cold and Flu Relief Softgels
NDC: 50066-312 | Form: CAPSULE, LIQUID FILLED
Manufacturer: Genomma Lab USA
Category: otc | Type: HUMAN OTC DRUG LABEL
Date: 20230110

ACTIVE INGREDIENTS: ACETAMINOPHEN 325 mg/1 1; DEXTROMETHORPHAN HYDROBROMIDE 10 mg/1 1; PHENYLEPHRINE HYDROCHLORIDE 5 mg/1 1
INACTIVE INGREDIENTS: GELATIN, UNSPECIFIED; GLYCERIN; POLYETHYLENE GLYCOL, UNSPECIFIED; POVIDONE, UNSPECIFIED; PROPYLENE GLYCOL; WATER

Tukol® Day Time Cold and Flu Relief Softgels

Drug Facts

ACTIVE INGREDIENT

Active ingredients (in each softgel) | Purpose
Acetaminophen 325 mg | Pain reliever/fever reducer
Dextromethorphan HBr 10 mg | Cough suppressant
Phenylephrine HCl 5 mg | Nasal decongestant

Uses

temporarily relieves common cold and flu symptoms:

- nasal congestion
- cough due to minor throat and bronchial irritation
- sore throat
- headache
- minor aches and pains
- fever

Warnings

Liver warning

This product contains acetaminophen. Severe liver damage may occur if you take

- more than 4 doses in 24 hours, which is the maximum daily amount
- with other drugs containing acetaminophen
- 3 or more alcoholic drinks every day while using this product

Allergy alert

Acetaminophen may cause severe skin reactions. Symptoms may include:

- skin reddening
- blisters
- rash If skin reaction occurs, stop use and seek medical help right away.

Sore throat warning

If sore throat is severe, persists for more than 2 days, is accompanied or followed by fever, headache, rash, nausea, or vomiting, consult a doctor promptly.

Do not use

- with any other products containing acetaminophen (prescription or nonprescription). If you are not sure whether a drug contains acetaminophen, ask a doctor or pharmacist
- if you are now taking a prescription monoamine oxidase inhibitor (MAOI) (certain drugs for depression, psychiatric or emotional conditions, or Parkinson's disease), or for 2 weeks after stopping the MAOI drugs. If you do not know if your prescription drug contains an MAOI, ask a doctor or pharmacist before taking this product.

Ask a doctor before use if you have

- liver disease
- heart disease
- thyroid disease
- diabetes
- high blood pressure
- trouble urinating due to enlarged prostate gland
- cough that occurs with too much phlegm (mucus)
- persistent or chronic cough as occurs with smoking, asthma, or emphysema

Ask a doctor or pharmacist before use if you are

- taking the blood thinning drug warfarin

When using this product

- do not exceed recommended dosage

Stop use and ask a doctor if

- you get nervous, dizzy or sleepless
- symptoms get worse or last more than 5 days (children) or 7 days (adults)
- fever gets worse or lasts more than 3 days
- redness or swelling is present
- new symptoms occur
- cough comes back or occurs with rash or headache that lasts.
- a skin reaction occurs. These could be signs of a serious condition.

PREGNANCY OR BREAST FEEDING

If pregnant or breast-feeding, ask a health professional before use

Keep out of reach of children. In case of accidental overdose, get medical help or contact a Poison Control Center right away. Quick medical attention is critical for adults as well as for children, even if you do not notice any signs or symptoms.

Directions

- take only as directed (see Warnings)
- do not exceed 4 doses per 24 hours
  Adults and children 12 years and over: take 2 softgels with water every 4 hours
  Children 4 to under 12 years: Ask a doctor
  Children under 4 years: Do not use
- When using Day Time or Night Time products, carefully read each label to ensure correct dosing

Other information

- store at room temperature 20-25°C (68-77°F)

Inactive Ingredients

FD&C Red #40, FD&C Yellow #6, Gelatin, Glycerin, Polyethylene glycol, Povidone, Propylene glycol, Purified Water, Sorbitol sorbitan solution, Titanium dioxide.

Questions or comments?

Call toll free 1-877-994-3666

Weekdays from 8 am to 6 pm

Distributed by:
Genomma Lab USA, Inc.
Houston, TX 77098

PRINCIPAL DISPLAY PANEL - 24 Softgel Blister Pack Carton

NEW
Non Drowsy

Tukol®

DAY TIME
COLD AND FLU RELIEF

Acetaminophen / Dextromethorphan HBr /
Phenylephrine HCl

- COUGH
- FEVER
- SORE THROAT
- ACHES
- NASAL CONGESTION

24 Softgels